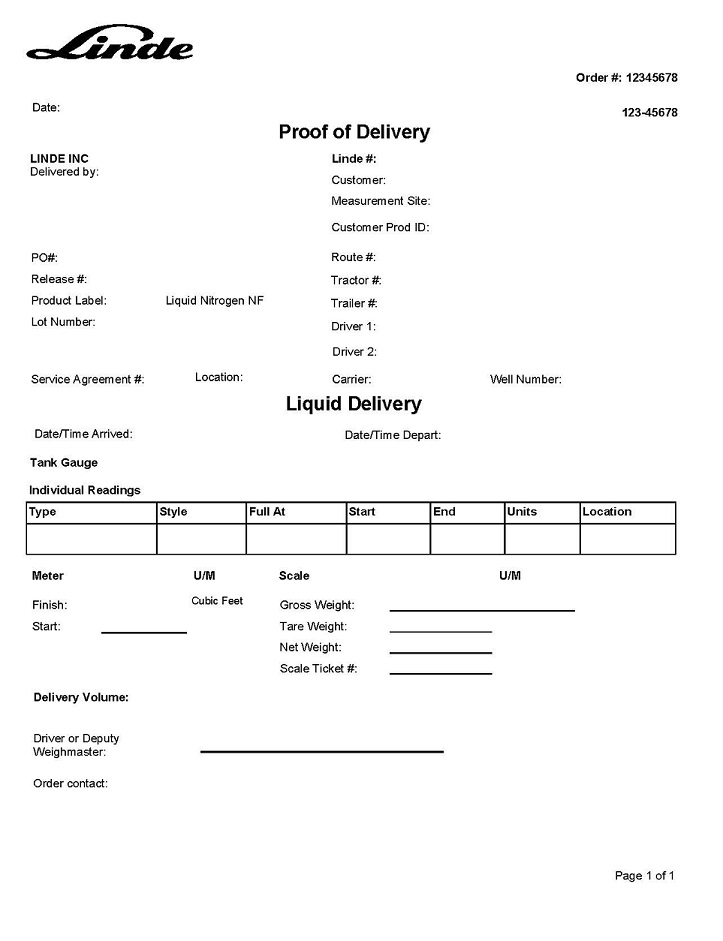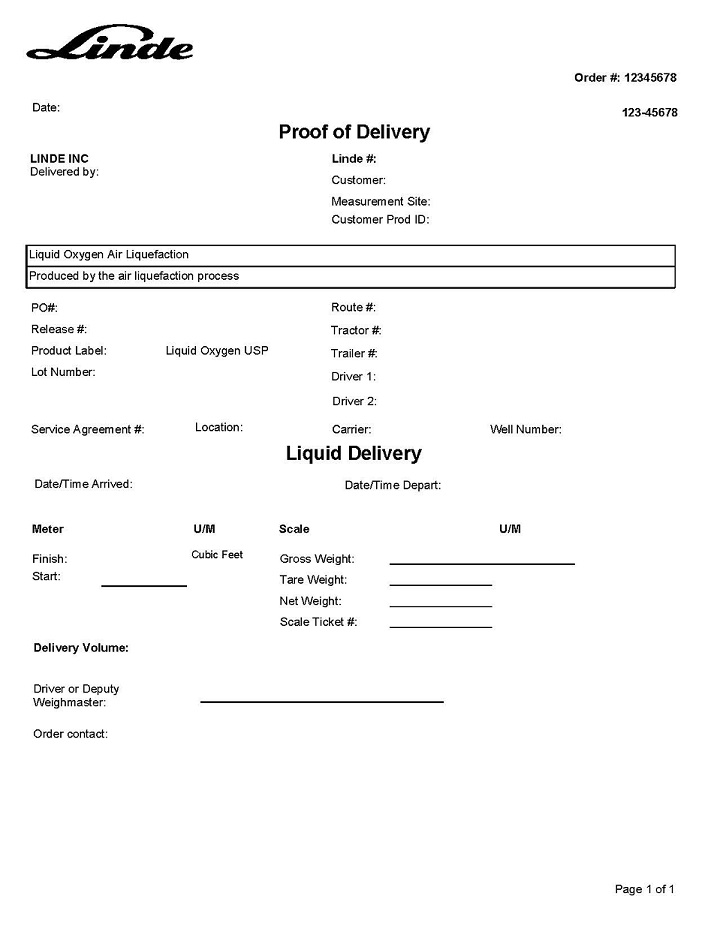 DRUG LABEL: Nitrogen
NDC: 11324-499 | Form: GAS
Manufacturer: Linde Puerto Rico B.V.
Category: prescription | Type: HUMAN PRESCRIPTION DRUG LABEL
Date: 20251231

ACTIVE INGREDIENTS: NITROGEN 990 mL/1 L

Liquid Oxygen USP Liquid Nitrogen NF Humacao, PR